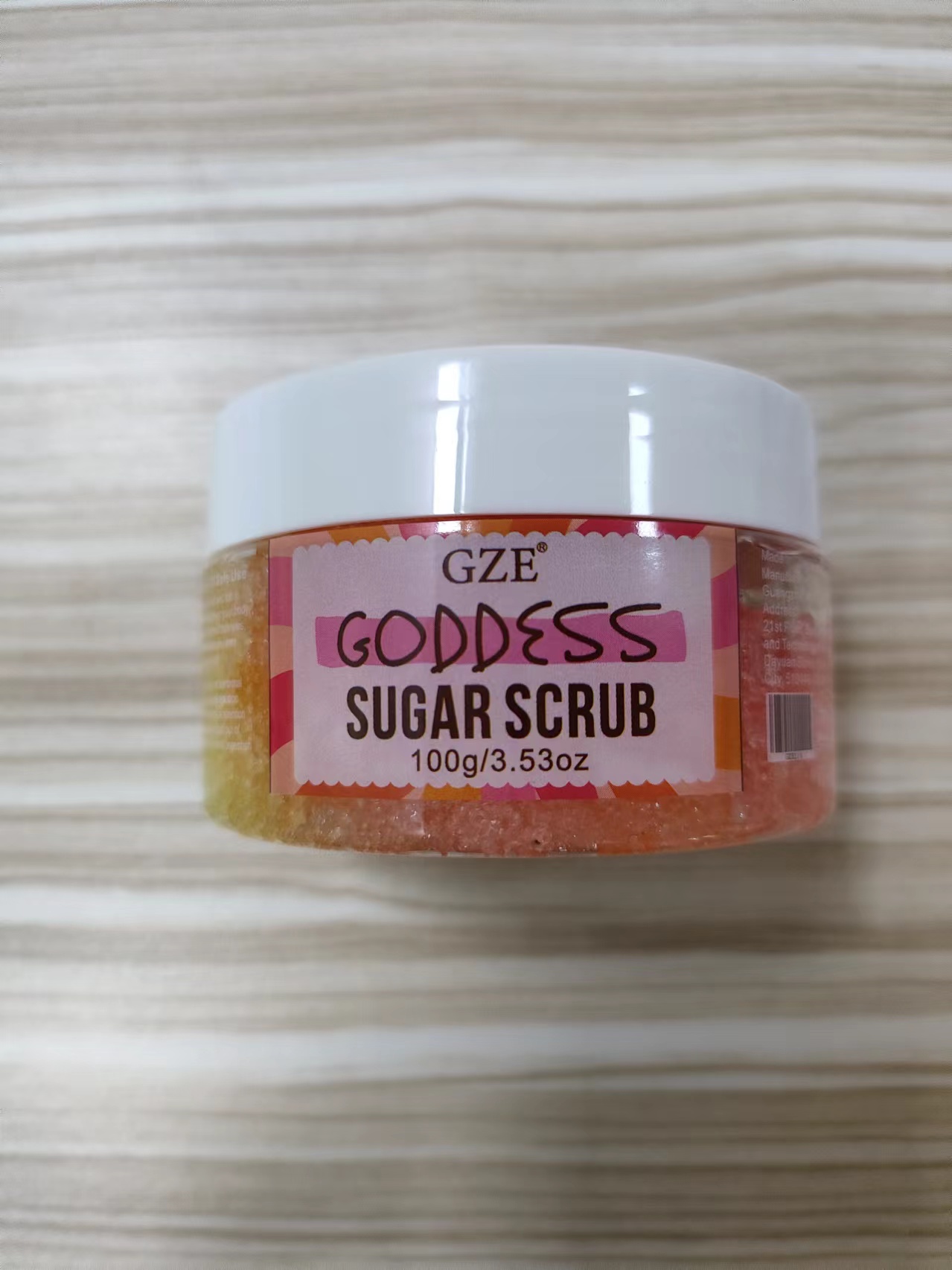 DRUG LABEL: GZE GODDESS SUGAR SCRUB
NDC: 74458-216 | Form: CAPSULE
Manufacturer: Guangzhou Yilong Cosmetics Co., Ltd
Category: otc | Type: HUMAN OTC DRUG LABEL
Date: 20241111

ACTIVE INGREDIENTS: SUCROSE 15 g/100 g
INACTIVE INGREDIENTS: POLYSORBATE 20; AQUA; CI 19140; LIMONENE, (+)-; CI 14700; CI 17200; SODIUM SULFATE; GLYCERIN; SODIUM CHLORIDE; SILICON DIOXIDE

GZE GODDESS SUGAR SCRUB

INACTIVE INGREDIENT

Glycerin

Sodium Chloride

Sodium Sulfate

Sucrose

Polysorbate 20

Aqua

Parfum

CI 19140

CI 14700

CI 17200

Limonene

PURPOSE

Exfoliating.

INDICATIONS AND USAGE

Wash your body, take an appropriate amount of Scrub and apply it to your skin, gently rub in a circle, and finally rinse it off with water, once a month.

WARNINGS

For external use only.

Stop use and ask a doctor if rash occurs.

Do not use on damaged or broken skin.

When using this product keep out of eyes. Rinse with water to remove.

Keep out of reach of children. If swallowed, get medical help or contact a Poison Control Center right away.

DOSAGE AND ADMINISTRATION

Wash your body, take an appropriate amount of Scrub and apply it to your skin, gently rub in a circle, and finally rinse it off with water, once a month.